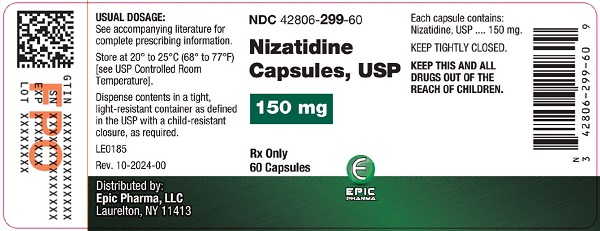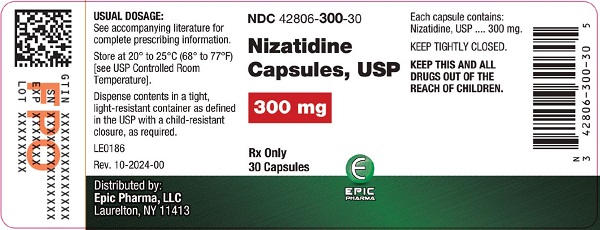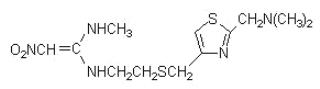 DRUG LABEL: Nizatidine
NDC: 42806-299 | Form: CAPSULE
Manufacturer: Epic Pharma, LLC
Category: prescription | Type: HUMAN PRESCRIPTION DRUG LABEL
Date: 20250102

ACTIVE INGREDIENTS: Nizatidine 150 mg/1 1
INACTIVE INGREDIENTS: CROSCARMELLOSE SODIUM; STARCH, CORN; DIMETHICONE, UNSPECIFIED; POVIDONE, UNSPECIFIED; TALC; GELATIN, UNSPECIFIED; FERRIC OXIDE YELLOW; TITANIUM DIOXIDE; ALCOHOL; AMMONIA; BUTYL ALCOHOL; FERROSOFERRIC OXIDE; ISOPROPYL ALCOHOL; PROPYLENE GLYCOL; POTASSIUM HYDROXIDE; SHELLAC

NIZATIDINE CAPSULES, USP

DESCRIPTION

Nizatidine, USP is a histamine H2-receptor antagonist. Chemically, it is N-[2-[[[2-[(dimethylamino)methyl]-4-thiazolyl]methyl]thio]ethyl]-N'-methyl-2-nitro-1,1-ethenediamine.

The structural formula is as follows:

Nizatidine, USP has the empirical formula C12H21N5O2S2 representing a molecular weight of 331.46. It is an off white to buff crystalline solid that is soluble in water. Nizatidine has a bitter taste and mild sulfur-like odor. Each capsule for oral administration contains nizatidine, USP, 150 mg (0.45 mmol) or 300 mg (0.91 mmol), croscarmellose sodium, corn starch, dimethicone, partially pregelatinized starch (Corn), povidone, talc. Ingredients for 150 mg capsule shell: gelatin, iron oxide yellow, titanium dioxide. Ingredients for 300 mg capsule shell: D&C red 28, FD&C blue 1, FD&C yellow 6, gelatin, titanium dioxide. Ingredients for 150 mg capsule shell: gelatin, iron oxide yellow, titanium dioxide. Ingredients for 300 mg capsule shell: D&C red 28, FD&C blue 1, FD&C yellow 6, gelatin, titanium dioxide. Ingredients for the ink used in capsule printing are ammonia solution concentrated, butyl alcohol, black iron oxide, dehydrated alcohol, isopropyl alcohol, propylene glycol, potassium hydroxide, shellac.

CLINICAL PHARMACOLOGY

Nizatidine is a competitive, reversible inhibitor of histamine at the histamine H2-receptors, particularly those in the gastric parietal cells.

Antisecretory Activity

Effects on Acid Secretion

Nizatidine significantly inhibited nocturnal gastric acid secretion for up to 12 hours. Nizatidine also significantly inhibited gastric acid secretion stimulated by food, caffeine, betazole, and pentagastrin (Table 1).

Table 1.—Effect of Oral Nizatidine on Gastric Acid Secretion
 | Time After Dose (h) | % Inhibition of Gastric Acid Output by Dose (mg)
 |  | 20-50 | 75 | 100 | 150 | 300
Nocturnal | Up to 10 | 57 |  | 73 |  | 90
Betazole | Up to 3 |  | 93 |  | 100 | 99
Pentagastrin | Up to 6 |  | 25 |  | 64 | 67
Meal | Up to 4 | 41 | 64 |  | 98 | 97
Caffeine | Up to 3 |  | 73 |  | 85 | 96

Effects on Other Gastrointestinal Secretions

Pepsin

Oral administration of 75 to 300 mg of nizatidine did not affect pepsin activity in gastric secretions. Total pepsin output was reduced in proportion to the reduced volume of gastric secretions.

Intrinsic factor

Oral administration of 75 to 300 mg of nizatidine increased betazole-stimulated secretion of intrinsic factor.

Serum gastrin

Nizatidine had no effect on basal serum gastrin. No rebound of gastrin secretion was observed when food was ingested 12 hours after administration of nizatidine.

Other Pharmacologic Actions

Hormones

Nizatidine was not shown to affect the serum concentrations of gonadotropins, prolactin, growth hormone, antidiuretic hormone, cortisol, triiodothyronine, thyroxin, testosterone, 5α-dihydrotestosterone, androstenedione, or estradiol.

Nizatidine had no demonstrable antiandrogenic action.

Pharmacokinetics

The absolute oral bioavailability of nizatidine exceeds 70%. Peak plasma concentrations (700 to 1,800 mcg/L for a 150-mg dose and 1,400 to 3,600 mcg/L for a 300-mg dose) occur from 0.5 to 3 hours following the dose. A concentration of 1,000 mcg/L is equivalent to 3 µmol/L; a dose of 300 mg is equivalent to 905 µmoles. Plasma concentrations 12 hours after administration are less than 10 mcg/L. The elimination half-life is 1 to 2 hours, plasma clearance is 40 to 60 L/h, and the volume of distribution is 0.8 to 1.5 L/kg. Because of the short half-life and rapid clearance of nizatidine, accumulation of the drug would not be expected in individuals with normal renal function who take either 300 mg once daily at bedtime or 150 mg twice daily. Nizatidine exhibits dose proportionality over the recommended dose range.

The oral bioavailability of nizatidine is unaffected by concomitant ingestion of propantheline. Antacids consisting of aluminum and magnesium hydroxides with simethicone decrease the absorption of nizatidine by about 10%. With food, the AUC and Cmax increase by approximately 10%.

In humans, less than 7% of an oral dose is metabolized as N2-monodesmethylnizatidine, an H2-receptor antagonist, which is the principal metabolite excreted in the urine. Other likely metabolites are the N2-oxide (less than 5% of the dose) and the S-oxide (less than 6% of the dose).

More than 90% of an oral dose of nizatidine is excreted in the urine within 12 hours. About 60% of an oral dose is excreted as unchanged drug. Renal clearance is about 500 mL/min, which indicates excretion by active tubular secretion. Less than 6% of an administered dose is eliminated in the feces.

Moderate to severe renal impairment significantly prolongs the half-life and decreases the clearance of nizatidine. In individuals who are functionally anephric, the half-life is 3.5 to 11 hours, and the plasma clearance is 7 to 14 L/h. To avoid accumulation of the drug in individuals with clinically significant renal impairment, the amount and/or frequency of doses of nizatidine should be reduced in proportion to the severity of dysfunction (see DOSAGE AND ADMINISTRATION).

Approximately 35% of nizatidine is bound to plasma protein, mainly to α1-acid glycoprotein. Warfarin, diazepam, acetaminophen, propantheline, phenobarbital, and propranolol did not affect plasma protein binding of nizatidine in vitro.

Clinical Trials

1. Active Duodenal Ulcer

In multicenter, double-blind, placebo-controlled studies in the United States, endoscopically diagnosed duodenal ulcers healed more rapidly following administration of nizatidine, 300 mg h.s. or 150 mg b.i.d., than with placebo (Table 2). Lower doses, such as 100 mg h.s., had slightly lower effectiveness.

Table 2.—Healing Response of Ulcers to Nizatidine
 | Nizatidine |  |  |  | Placebo
 | 300 mg h.s. |  | 150 mg b.i.d.
 | Number Entered | Healed/ Evaluable | Number Entered | Healed/ Evaluable | Number Entered | Healed/ Evaluable
STUDY 1
Week 2 |  |  | 276 | 93/265 (35%) | 279 | 55/260 (21%)
Week 4 |  |  |  | 198/259 (76%) |  | 95/243 (39%)
STUDY 2
Week 2 | 108 | 24/103 (23%) | 106 | 27/101 (27%) | 101 | 9/93 (10%)
Week 4 |  | 65/97 (67%) |  | 66/97 (68%) |  | 24/84 (29%)
STUDY 3
Week 2 | 92 | 22/90 (24%) |  |  | 98 | 13/92 (14%)
Week 4 |  | 52/85 (61%) |  |  |  | 29/88 (33%)
Week 8 |  | 68/83 (82%) |  |  |  | 39/79 (49%)

*P less than 0.01 as compared with placebo.

†P less than 0.05 as compared with placebo.

2. Maintenance of Healed Duodenal Ulcer

Treatment with a reduced dose of nizatidine has been shown to be effective as maintenance therapy following healing of active duodenal ulcers. In multicenter, double-blind, placebo-controlled studies conducted in the United States, 150 mg of nizatidine taken at bedtime resulted in a significantly lower incidence of duodenal ulcer recurrence in patients treated for up to 1 year (Table 3).

Table 3. Percentage of Ulcers Recurring by 3, 6, and 12 Months in Double-Blind Studies Conducted in the United States
Month | Nizatidine, 150 mg h.s. | Placebo
3 | 13% (28/208) | 40% (82/204)
6 | 24% (45/188) | 57% (106/187)
12 | 34% (57/166) | 64% (112/175)

*P less than 0.001 as compared with placebo.

3. Gastroesophageal Reflux Disease (GERD)

In 2 multicenter, double-blind, placebo-controlled clinical trials performed in the United States and Canada, nizatidine was more effective than placebo in improving endoscopically diagnosed esophagitis and in healing erosive and ulcerative esophagitis.

In patients with erosive or ulcerative esophagitis, 150 mg b.i.d. of nizatidine given to 88 patients compared with placebo in 98 patients in Study 1 yielded a higher healing rate at 3 weeks (16% vs 7%) and at 6 weeks (32% vs 16%, P<0.05). Of 99 patients on nizatidine and 94 patients on placebo, Study 2 at the same dosage yielded similar results at 6 weeks (21% vs 11%, P<0.05) and at 12 weeks (29% vs 13%, P<0.01).

In addition, relief of associated heartburn was greater in patients treated with nizatidine. Patients treated with nizatidine consumed fewer antacids than did patients treated with placebo.

4. Active Benign Gastric Ulcer

In a multicenter, double-blind, placebo-controlled study conducted in the United States and Canada, endoscopically diagnosed benign gastric ulcers healed significantly more rapidly following administration of nizatidine than of placebo (Table 4).

Table
Week | Treatment | Healing Rate | vs. Placebo p-value
4 | Niz 300 mg h.s. | 52/153 (34%) | 0.342
4 | Niz 150 mg b.i.d. | 65/151 (43%) | 0.022
4 | Placebo | 48/151 (32%)
8 | Niz 300 mg h.s. | 99/153 (65%) | 0.011
8 | Niz 150 mg b.i.d. | 105/151 (70%) | less than 0.001
8 | Placebo | 78/151 (52%)

*P-values are one-sided, obtained by Chi-square test, and not adjusted for multiple comparisons

In a multicenter, double-blind, comparator-controlled study in Europe, healing rates for patients receiving nizatidine (300 mg h.s. or 150 mg b.i.d.) were equivalent to rates for patients receiving a comparator drug, and statistically superior to historical placebo control rates.

INDICATIONS AND USAGE

Nizatidine capsules are indicated for up to 8 weeks for the treatment of active duodenal ulcer. In most patients, the ulcer will heal within 4 weeks.

Nizatidine capsules are indicated for maintenance therapy for duodenal ulcer patients at a reduced dosage of 150 mg h.s. after healing of an active duodenal ulcer. The consequences of continuous therapy with nizatidine for longer than 1 year are not known.

Nizatidine capsules are indicated for up to 12 weeks for the treatment of endoscopically diagnosed esophagitis, including erosive and ulcerative esophagitis, and associated heartburn due to GERD.

Nizatidine capsules are indicated for up to 8 weeks for the treatment of active benign gastric ulcer. Before initiating therapy, care should be taken to exclude the possibility of malignant gastric ulceration.

CONTRAINDICATION

Nizatidine capsules are contraindicated in patients with known hypersensitivity to the drug. Because cross sensitivity in this class of compounds has been observed, H2-receptor antagonists, including nizatidine, should not be administered to patients with a history of hypersensitivity to other H2-receptor antagonists.

PRECAUTIONS

General

1. Symptomatic response to nizatidine therapy does not preclude the presence of gastric malignancy.
2. Because nizatidine is excreted primarily by the kidney, dosage should be reduced in patients with moderate to severe renal insufficiency (see DOSAGE AND ADMINISTRATION).
3. Pharmacokinetic studies in patients with hepatorenal syndrome have not been done. Part of the dose of nizatidine is metabolized in the liver. In patients with normal renal function and uncomplicated hepatic dysfunction, the disposition of nizatidine is similar to that in normal subjects.

Laboratory Tests

False-positive tests for urobilinogen with Multistix® may occur during therapy with nizatidine.

Drug Interactions

No interactions have been observed between nizatidine and theophylline, chlordiazepoxide, lorazepam, lidocaine, phenytoin, and warfarin. Nizatidine does not inhibit the cytochrome P-450-linked drug-metabolizing enzyme system; therefore, drug interactions mediated by inhibition of hepatic metabolism are not expected to occur. In patients given very high doses (3,900 mg) of aspirin daily, increases in serum salicylate levels were seen when nizatidine, 150 mg b.i.d., was administered concurrently.

Carcinogenesis, Mutagenesis, Impairment of Fertility

A 2-year oral carcinogenicity study in rats with doses as high as 500 mg/kg/day (about 80 times the recommended daily therapeutic dose) showed no evidence of a carcinogenic effect. There was a dose-related increase in the density of enterochromaffin-like (ECL) cells in the gastric oxyntic mucosa. In a 2-year study in mice, there was no evidence of a carcinogenic effect in male mice; although hyperplastic nodules of the liver were increased in the high-dose males as compared with placebo. Female mice given the high dose of nizatidine (2,000 mg/kg/day, about 330 times the human dose) showed marginally statistically significant increases in hepatic carcinoma and hepatic nodular hyperplasia with no numerical increase seen in any of the other dose groups. The rate of hepatic carcinoma in the high-dose animals was within the historical control limits seen for the strain of mice used. The female mice were given a dose larger than the maximum tolerated dose, as indicated by excessive (30%) weight decrement as compared with concurrent controls and evidence of mild liver injury (transaminase elevations). The occurrence of a marginal finding at high dose only in animals given an excessive and somewhat hepatotoxic dose, with no evidence of a carcinogenic effect in rats, male mice, and female mice (given up to 360 mg/kg/day, about 60 times the human dose), and a negative mutagenicity battery are not considered evidence of a carcinogenic potential for nizatidine.

Nizatidine was not mutagenic in a battery of tests performed to evaluate its potential genetic toxicity, including bacterial mutation tests, unscheduled DNA synthesis, sister chromatid exchange, mouse lymphoma assay, chromosome aberration tests, and a micronucleus test.

In a 2-generation, perinatal and postnatal fertility study in rats, doses of nizatidine up to 650 mg/kg/day produced no adverse effects on the reproductive performance of parental animals or their progeny.

Pregnancy

Teratogenic Effects

Pregnancy category B

Oral reproduction studies in pregnant rats at doses up to 1500 mg/kg/day (9000 mg/m^2/day, 40.5 times the recommended human dose based on body surface area) and in pregnant rabbits at doses up to 275 mg/kg/day (3245 mg/m^2/day, 14.6 times the recommended human dose based on body surface area) have revealed no evidence of impaired fertility or harm to the fetus due to nizatidine. There are, however, no adequate and well-controlled studies in pregnant women. Because animal reproduction studies are not always predictive of human response, this drug should be used during pregnancy only if clearly needed.

Nursing Mothers

Studies conducted in lactating women have shown that 0.1% of the administered oral dose of nizatidine is secreted in human milk in proportion to plasma concentrations. Because of the growth depression in pups reared by lactating rats treated with nizatidine, a decision should be made whether to discontinue nursing or discontinue the drug, taking into account the importance of the drug to the mother.

Pediatric Use

Safety and effectiveness in pediatric patients have not been established.

Geriatric Use

Of the 955 patients in clinical studies who were treated with nizatidine, 337 (35.3%) were 65 and older. No overall differences in safety or effectiveness were observed between these and younger subjects. Other reported clinical experience has not identified differences in responses between the elderly and younger patients, but greater sensitivity of some older individuals cannot be ruled out.

This drug is known to be substantially excreted by the kidney, and the risk of toxic reactions to this drug may be greater in patients with impaired renal function. Because elderly patients are more likely to have decreased renal function, care should be taken in dose selection, and it may be useful to monitor renal function (see DOSAGE AND ADMINISTRATION).

ADVERSE REACTIONS

Worldwide, controlled clinical trials of nizatidine included over 6,000 patients given nizatidine in studies of varying durations. Placebo-controlled trials in the United States and Canada included over 2,600 patients given nizatidine and over 1,700 given placebo. Among the adverse events in these placebo-controlled trials, anemia (0.2% vs 0%) and urticaria (0.5% vs 0.1%) were significantly more common in the nizatidine group.

Incidence in Placebo-Controlled Clinical Trials in the United States and Canada

Table 5 lists adverse events that occurred at a frequency of 1% or more among nizatidine-treated patients who participated in placebo-controlled trials. The cited figures provide some basis for estimating the relative contribution of drug and nondrug factors to the side-effect incidence rate in the population studied.

Table 5. Incidence of Treatment-Emergent Adverse Events in Placebo-Controlled Clinical Trials in the United States and Canada
 | Percentage of Patients Reporting Event
Body System/Adverse Event [Events reported by at least 1% of nizatidine-treated patients are included.] | Nizatidine (N=2,694) | Placebo (N=1,729)
Body as a Whole
Headache | 16.6 | 15.6
Abdominal pain | 7.5 | 12.5
Pain | 4.2 | 3.8
Asthenia | 3.1 | 2.9
Back pain | 2.4 | 2.6
Chest pain | 2.3 | 2.1
Infection | 1.7 | 1.1
Fever | 1.6 | 2.3
Surgical procedure | 1.4 | 1.5
Injury, accident | 1.2 | 0.9
Digestive
Diarrhea | 7.2 | 6.9
Nausea | 5.4 | 7.4
Flatulence | 4.9 | 5.4
Vomiting | 3.6 | 5.6
Dyspepsia | 3.6 | 4.4
Constipation | 2.5 | 3.8
Dry mouth | 1.4 | 1.3
Nausea and vomiting | 1.2 | 1.9
Anorexia | 1.2 | 1.6
Gastrointestinal disorder | 1.1 | 1.2
Tooth disorder | 1.0 | 0.8
Musculoskeletal
Myalgia | 1.7 | 1.5
Nervous
Dizziness | 4.6 | 3.8
Insomnia | 2.7 | 3.4
Abnormal dreams | 1.9 | 1.9
Somnolence | 1.9 | 1.6
Anxiety | 1.6 | 1.4
Nervousness | 1.1 | 0.8
Respiratory
Rhinitis | 9.8 | 9.6
Pharyngitis | 3.3 | 3.1
Sinusitis | 2.4 | 2.1
Cough, increased | 2.0 | 2.0
Skin and Appendages
Rash | 1.9 | 2.1
Pruritus | 1.7 | 1.3
Special Senses
Amblyopia | 1.0 | 0.9

A variety of less common events were also reported; it was not possible to determine whether these were caused by nizatidine.

Hepatic

Hepatocellular injury, evidenced by elevated liver enzyme tests (SGOT [AST], SGPT [ALT], or alkaline phosphatase), occurred in some patients and was possibly or probably related to nizatidine. In some cases, there was marked elevation of SGOT, SGPT enzymes (greater than 500 IU/L) and, in a single instance, SGPT was greater than 2,000 IU/L. The overall rate of occurrences of elevated liver enzymes and elevations to 3 times the upper limit of normal, however, did not significantly differ from the rate of liver enzyme abnormalities in placebo-treated patients. All abnormalities were reversible after discontinuation of nizatidine. Since market introduction, hepatitis and jaundice have been reported. Rare cases of cholestatic or mixed hepatocellular and cholestatic injury with jaundice have been reported with reversal of the abnormalities after discontinuation of nizatidine.

Cardiovascular

In clinical pharmacology studies, short episodes of asymptomatic ventricular tachycardia occurred in 2 individuals administered nizatidine and in 3 untreated subjects.

CNS

Rare cases of reversible mental confusion have been reported.

Endocrine

Clinical pharmacology studies and controlled clinical trials showed no evidence of antiandrogenic activity due to nizatidine. Impotence and decreased libido were reported with similar frequency by patients who received nizatidine and by those given placebo. Rare reports of gynecomastia occurred.

Hematologic

Anemia was reported significantly more frequently in nizatidine- than in placebo-treated patients. Fatal thrombocytopenia was reported in a patient who was treated with nizatidine and another H2-receptor antagonist. On previous occasions, this patient had experienced thrombocytopenia while taking other drugs. Rare cases of thrombocytopenic purpura have been reported.

Integumental

Sweating and urticaria were reported significantly more frequently in nizatidine than in placebo-treated patients. Rash and exfoliative dermatitis were also reported. Vasculitis has been reported rarely.

Hypersensitivity

As with other H2-receptor antagonists, rare cases of anaphylaxis following administration of nizatidine have been reported. Rare episodes of hypersensitivity reactions (eg, bronchospasm, laryngeal edema, rash, and eosinophilia) have been reported.

Body as a Whole

Serum sickness-like reactions have occurred rarely in conjunction with nizatidine use.

Genitourinary

Reports of impotence have occurred.

Other

Hyperuricemia unassociated with gout or nephrolithiasis was reported. Eosinophilia, fever, and nausea related to nizatidine administration have been reported.

OVERDOSAGE

Overdoses of nizatidine have been reported rarely. The following is provided to serve as a guide should such an overdose be encountered.

Signs and Symptoms

There is little clinical experience with overdosage of nizatidine in humans. Test animals that received large doses of nizatidine have exhibited cholinergic-type effects, including lacrimation, salivation, emesis, miosis, and diarrhea. Single oral doses of 800 mg/kg in dogs and of 1,200 mg/kg in monkeys were not lethal. Intravenous median lethal doses in the rat and mouse were 301 mg/kg and 232 mg/kg respectively.

Treatment

To obtain up-to-date information about the treatment of overdose, a good resource is your certified Regional Poison Control Center. Telephone numbers of certified poison control centers are listed in the Physicians' Desk Reference (PDR). In managing overdosage, consider the possibility of multiple drug overdoses, interaction among drugs, and unusual drug kinetics in your patient.

If overdosage occurs, use of activated charcoal, emesis, or lavage should be considered along with clinical monitoring and supportive therapy. The ability of hemodialysis to remove nizatidine from the body has not been conclusively demonstrated; however, due to its large volume of distribution, nizatidine is not expected to be efficiently removed from the body by this method.

DOSAGE AND ADMINISTRATION

Active Duodenal Ulcer

The recommended oral dosage for adults is 300 mg once daily at bedtime. An alternative dosage regimen is 150 mg twice daily.

Maintenance of Healed Duodenal Ulcer

The recommended oral dosage for adults is 150 mg once daily at bedtime.

Gastroesophageal Reflux Disease

The recommended oral dosage in adults for the treatment of erosions, ulcerations, and associated heartburn is 150 mg twice daily.

Active Benign Gastric Ulcer

The recommended oral dosage is 300 mg given either as 150 mg twice daily or 300 mg once daily at bedtime. Prior to treatment, care should be taken to exclude the possibility of malignant gastric ulceration.

Dosage Adjustment for Patients With Moderate to Severe Renal Insufficiency

The dose for patients with renal dysfunction should be reduced as follows:

Active Duodenal Ulcer, GERD, and Benign Gastric Ulcer
Ccr | Dose
20-50 mL/min | 150 mg daily
less than 20 mL/min | 150 mg every other day
Maintenance Therapy
Ccr | Dose
20-50 mL/min | 150 mg every other day
less than 20 mL/min | 150 mg every 3 days

Some elderly patients may have creatinine clearances of less than 50 mL/min, and, based on pharmacokinetic data in patients with renal impairment, the dose for such patients should be reduced accordingly. The clinical effects of this dosage reduction in patients with renal failure have not been evaluated.

HOW SUPPLIED

Nizatidine Capsules USP, for oral administration, are available as

150 mg

#2 capsule, yellow opaque cap and white opaque body, imprinted "Є 299" in black ink on cap & body and supplied as:

NDC 42806-299-30 bottles of 30

NDC 42806-299-60 bottles of 60

300 mg

#1EL capsule, peach opaque cap and white opaque body, imprinted "Є 300" in black ink on cap & body and supplied as:

NDC 42806-300-30 bottles of 30

NDC 42806-300-60 bottles of 60

Store at 20° to 25°C (68° to 77°F) [see USP Controlled Room Temperature].

Dispense contents in a tight, light-resistant container as defined in the USP with a child-resistant closure, as required.

KEEP TIGHTLY CLOSED.

To report SUSPECTED ADVERSE REACTIONS, contact Epic Pharma, LLC at 1-888-374-2791 or FDA at 1-800-FDA-1088 or www.fda.gov/medwatch.

All brand names listed are the registered trademarks of their respective owners and are not trademarks of Epic Pharma, LLC.

Distributed by:

Epic Pharma, LLC

Laurelton, NY 11413

Rev. 10-2024-00

MF299REV10/24

LN0024